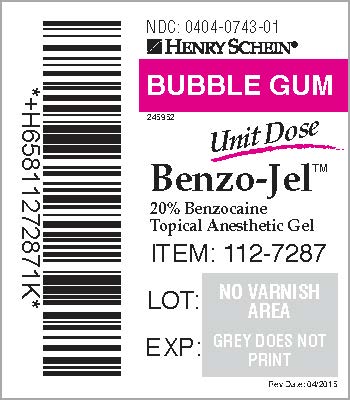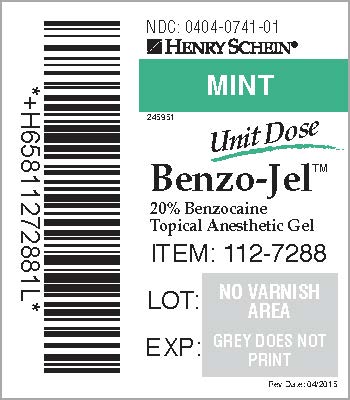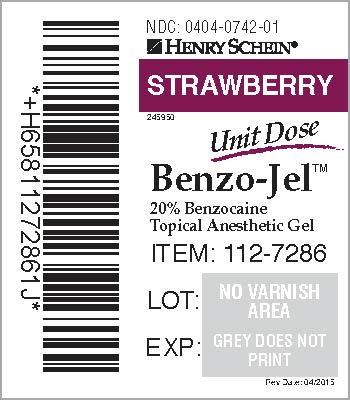 DRUG LABEL: Benzo-Jel 
NDC: 0404-0742 | Form: GEL
Manufacturer: Henry Schein, Inc.
Category: prescription | Type: HUMAN PRESCRIPTION DRUG LABEL
Date: 20181031

ACTIVE INGREDIENTS: Benzocaine 200 mg/1 g
INACTIVE INGREDIENTS: Polyethylene Glycol 400; Polyethylene Glycol 3350; Sucralose; Fd&c Red No. 40

Benzo-Jel™ Unit Dose

Storage: Store Benzo-Jel at controlled room temperature, between 59 and 86°F (15 and 30°C).

Caution: Federal law (USA) prohibits dispensing without a prescription.
Ingredients:
Active: Each gram of 20% Benzocaine gel contains 200mg of Benzocaine USP
Inactive:
Strawberry: Polyethylene Glycol 400, Polyethylene Glycol 3350, Sucralose, flavor, FD&C Red # 40
Bubble Gum: Polyethylene Glycol 400, Polyethylene Glycol 3350, Sucralose, flavor, D&C Red # 28
Mint: Polyethylene Glycol 400, Polyethylene Glycol 3350, Sucralose, flavors, D&C Green # 5
For professional use only.

REORDER #’S: Strawberry (#112-7286) Bubble Gum (#112-7287) Mint (#112-7288) NDC # 0404-0742-01 (Strawberry) NDC # 0404-0743-01 (Bubble Gum) NDC # 0404-0741-01 (Mint)

Distributed by (in US only):
HENRY SCHEIN, INC.
135 DURYEA ROAD
MELVILLE, NY 11747 USA
MADE IN USA
246001 Rev Date: 05/2015